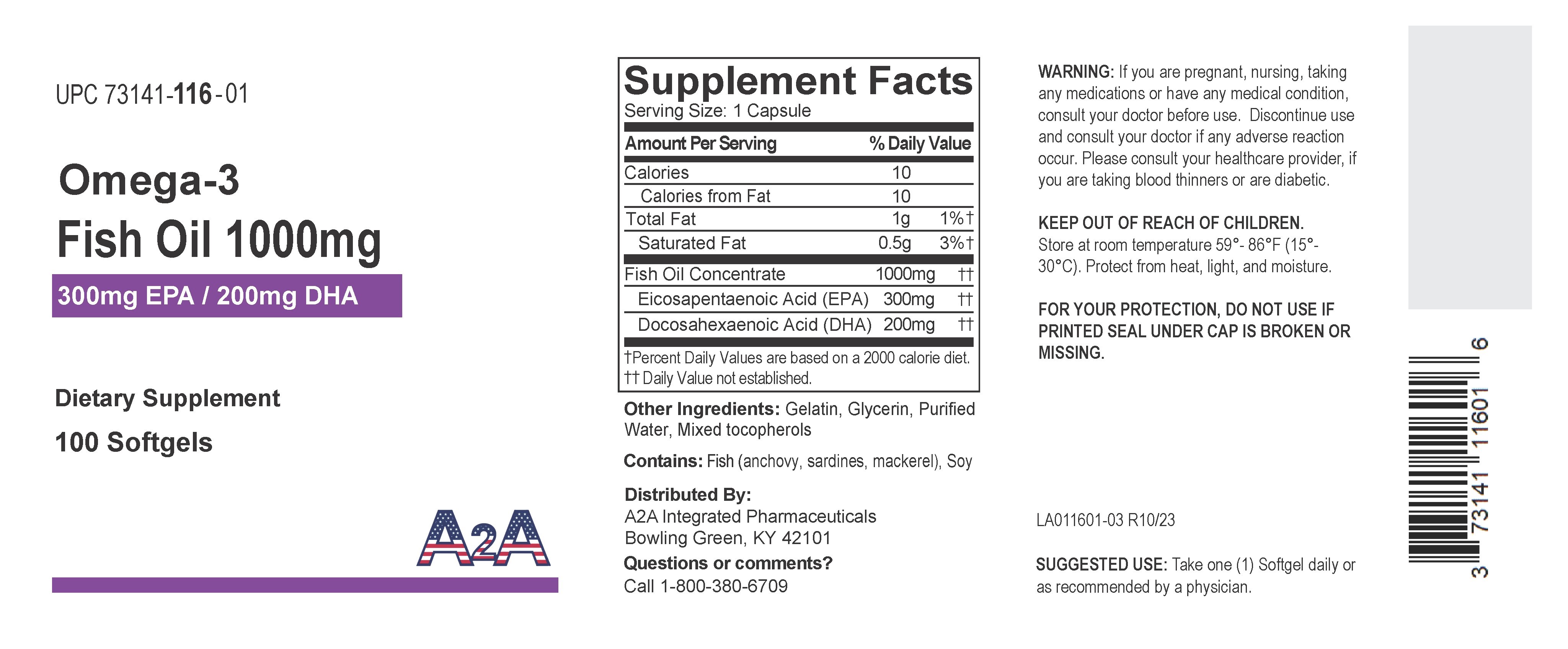 DRUG LABEL: A2A Omega-3
NDC: 73141-116 | Form: CAPSULE, GELATIN COATED
Manufacturer: A2A INTEGRATED PHARMACEUTICALS, LLC
Category: other | Type: DIETARY SUPPLEMENT
Date: 20240124

ACTIVE INGREDIENTS: Icosapent 300 mg/1 1; Doconexent 200 mg/1 1; FISH OIL 1000 mg/1 1
INACTIVE INGREDIENTS: Gelatin; glycerin; tocopherol; mackerel, unspecified; sardine, unspecified; anchovy, unspecified

OMEGA-3 FISH OIL 1000MG (300MG EPA/200MG DHA)

Supplement Facts

Dietary Supplement

Serving Size: 1 Capsule

Servings Per Container: 100

 | Amount Per Serving | % Daily Value
Calories | 10
Calories from Fat | 10
Total Fat | 1 g | 1%†
Saturated Fat | 0.5 g | 3%†
Fish body oil EPA (eicosapentaenoic acid) 300 mg DHA (docosahexaenoic acid) 200 mg | 1,000 mg††

Other ingredients: Gelatin, Glycerin, Purified Water, Mixed tocopherols

Contains: Fish (mackerel, sardines, anchovy), Soy

Directions

Take one (1) Softgel daily or as recommended by a physician.

Warning

If you are pregnant, nursing, taking any medications or have any medical condition, consult your doctor before use. Discontinue use and consult your doctor if any adverse reaction occur. Please consult your helathcare provider, if you are taking blood thinners or are diabetic.

SAFE HANDLING WARNING

Keep out of the reach of children.

- Store at 15-30°C (59-86°F).
- Protect from heat, light and moisture.

FOR YOUR PROTECTION, DO NOT USE IF PRINTED SEAL UNDER CAP IS BROKEN OR MISSING.

Distributed By:
A2A Integrated Pharmaceuticals
Bowling Green, KY 42101

Questions or comments?

Call 1-800-380-6709

PRINCIPAL DISPLAY PANEL - 100 Capsule Bottle Label

Omega-3

Fish Oil 1000mg

300mg EPA / 200mg DHA

Dietary Supplement

100 Softgels